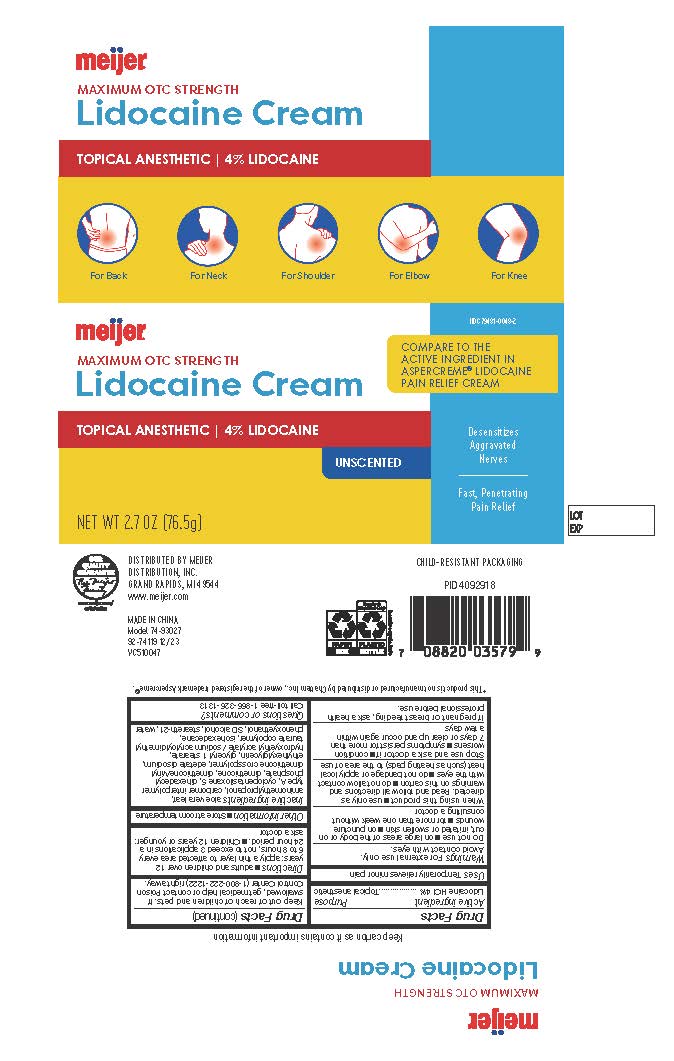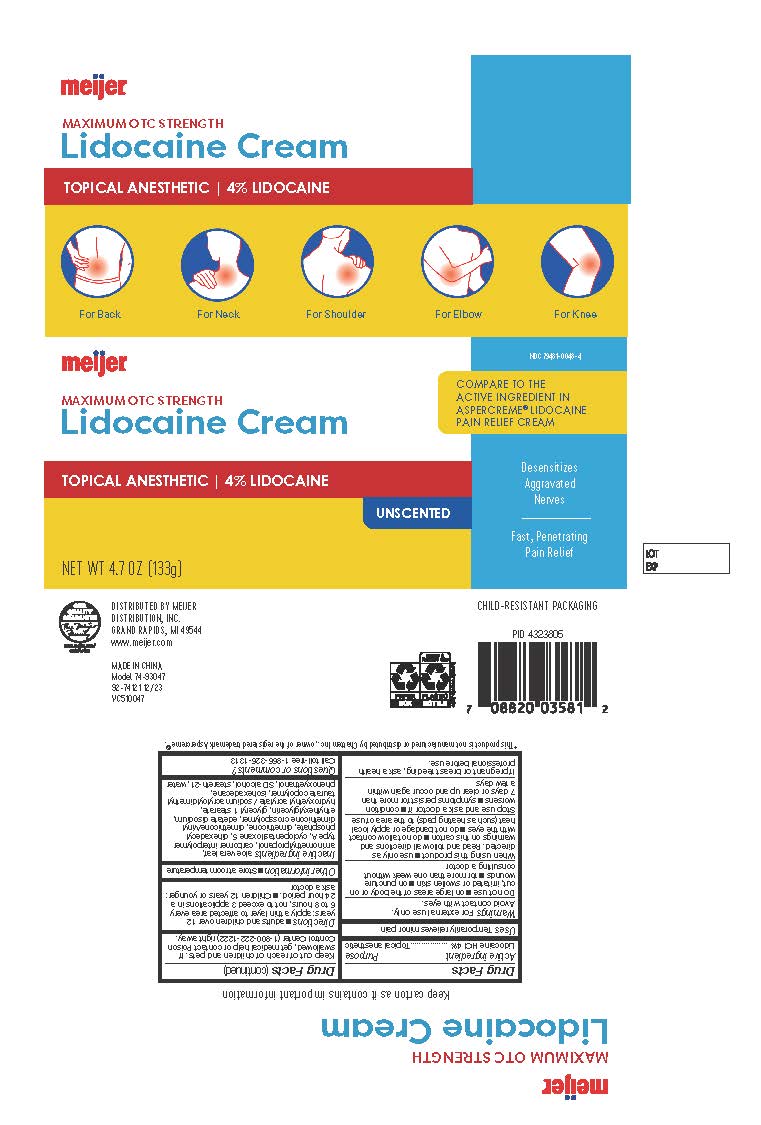 DRUG LABEL: Meijer Pain Relief Cream
NDC: 79481-0048 | Form: CREAM
Manufacturer: Meijer Distribution
Category: otc | Type: HUMAN OTC DRUG LABEL
Date: 20240327

ACTIVE INGREDIENTS: LIDOCAINE 4 g/100 g
INACTIVE INGREDIENTS: WATER; DIMETHICONE/VINYL DIMETHICONE CROSSPOLYMER (SOFT PARTICLE); HYDROXYETHYL ACRYLATE/SODIUM ACRYLOYLDIMETHYL TAURATE COPOLYMER (45000 MPA.S AT 1%); CYCLOMETHICONE 5; GLYCERYL 1-STEARATE; CARBOMER INTERPOLYMER TYPE A (55000 CPS); ALOE VERA LEAF; DIMETHICONE; EDETATE DISODIUM; ETHYLHEXYLGLYCERIN; ALCOHOL; PHENOXYETHANOL; DIHEXADECYL PHOSPHATE; STEARETH-21; ISOHEXADECANE; AMINOMETHYLPROPANOL

Meijer Pain Relief Cream with 4% Lidocaine

Active Ingredient

Lidocaine HCI 4%

Purpose

Topical anesthetic

Uses

Temporarily relieves minor pain

Warnings

For external use only.

Avoid contact with eyes.

Do not use

■ on large areas of the body or cut, irritated, or swollen skin

■ on puncture wounds

■ for more than one week without consulting a doctor

When using this product

■ use only as directed. Read and follow all directions and warnings on this carton

■ do not allow contact with the eyes

■ do not bandage or apply local heat (such as heating pads) to the area of use

Stop use and ask a doctor if

■ condition worsens

■ symptoms persist for more than 7 days or clear up and occur again within a few days

If pregnant or breastfeeding

ask a health professional before use

Keep out of reach of children and pets

If swallowed, get medical help or contact Poison Control Center (1-800-222-1222) right away.

Directions

■ adults and children over 12 years: apply a thin layer to affected area every 6 to 8 hours, not to exceed 3 applications in a
24 hour period.

■ Children 12 years or younger: ask a doctor

Other information

■ Store at room temperature

Inactive ingredient

aloe vera leaf, aminomethylpropanol, carbomer interpolymer type A, cyclopentasiloxane 5, dihexadecyl phosphate, dimethicone, dimethicone/vinyl dimethicone crosspolymer, edetate disodium, ethylhexylglycerin, glyceryl 1 stearate, hydroxyethyl acrylate / sodium acryloyldimethyl taurate copolymer, isohexadecane, phenoxyethanol, SD alcohol, steareth-21, water

Questions or comments?

Call toll-free 1-866-326-1313